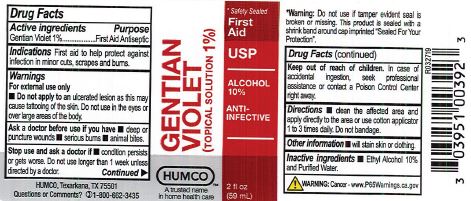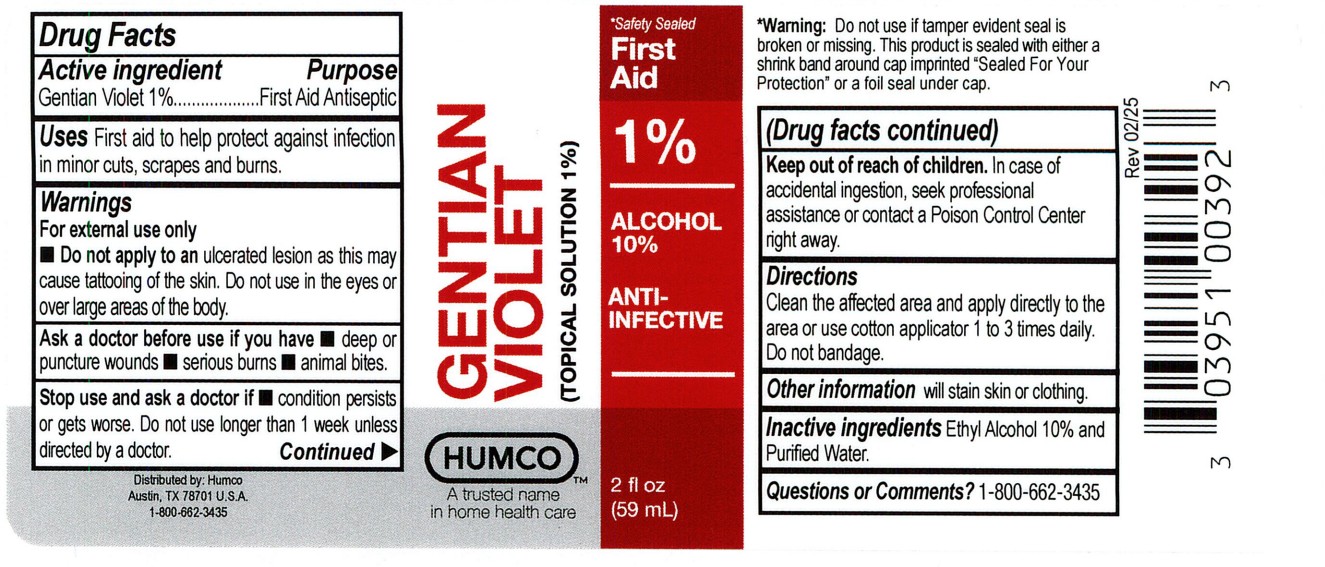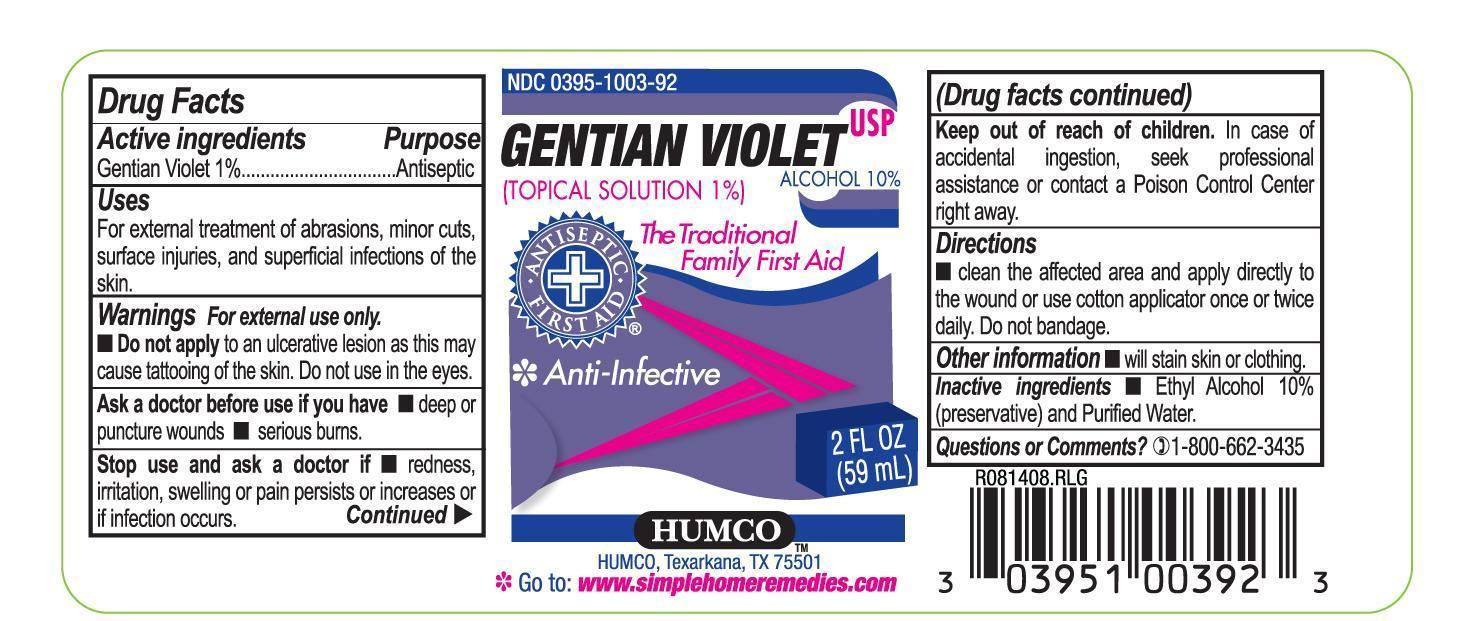 DRUG LABEL: Humco Gentian Violet 1%
NDC: 0395-1003 | Form: LIQUID
Manufacturer: Humco Holding Group, Inc.
Category: otc | Type: HUMAN OTC DRUG LABEL
Date: 20251211

ACTIVE INGREDIENTS: GENTIAN VIOLET 10 mg/1 mL
INACTIVE INGREDIENTS: ALCOHOL; WATER

Humco Gentian Violet 1%

Drug facts

Active Ingredient

Gentian Violet 1%

Purpose

Antiseptic

Uses

First aid to help protect against infection in minor cuts, scrapes and burns.

Warnings

For external use only.

Do not apply to an ulcerative lesion as this may cause tattooing of the skin. Do not use in the eyes.

Ask a doctor before use if

redness, irritation, swelling or pain persists or increases or if infection ocurs.

Keep out of reach of children.

In case of accidental ingestion, seek professional assistance or contact a Poison Control Center right away.

Directions

Clean the affected area and apply directly to the wound or use cotton applicator once or twice daily. Do not bandage.

Other information

will stain skin or clothing.

Inactive ingredients

Ethyl alcohol and purified water.

Questions or Comments?

1-800-662-3435

Principal Display Panel

Label